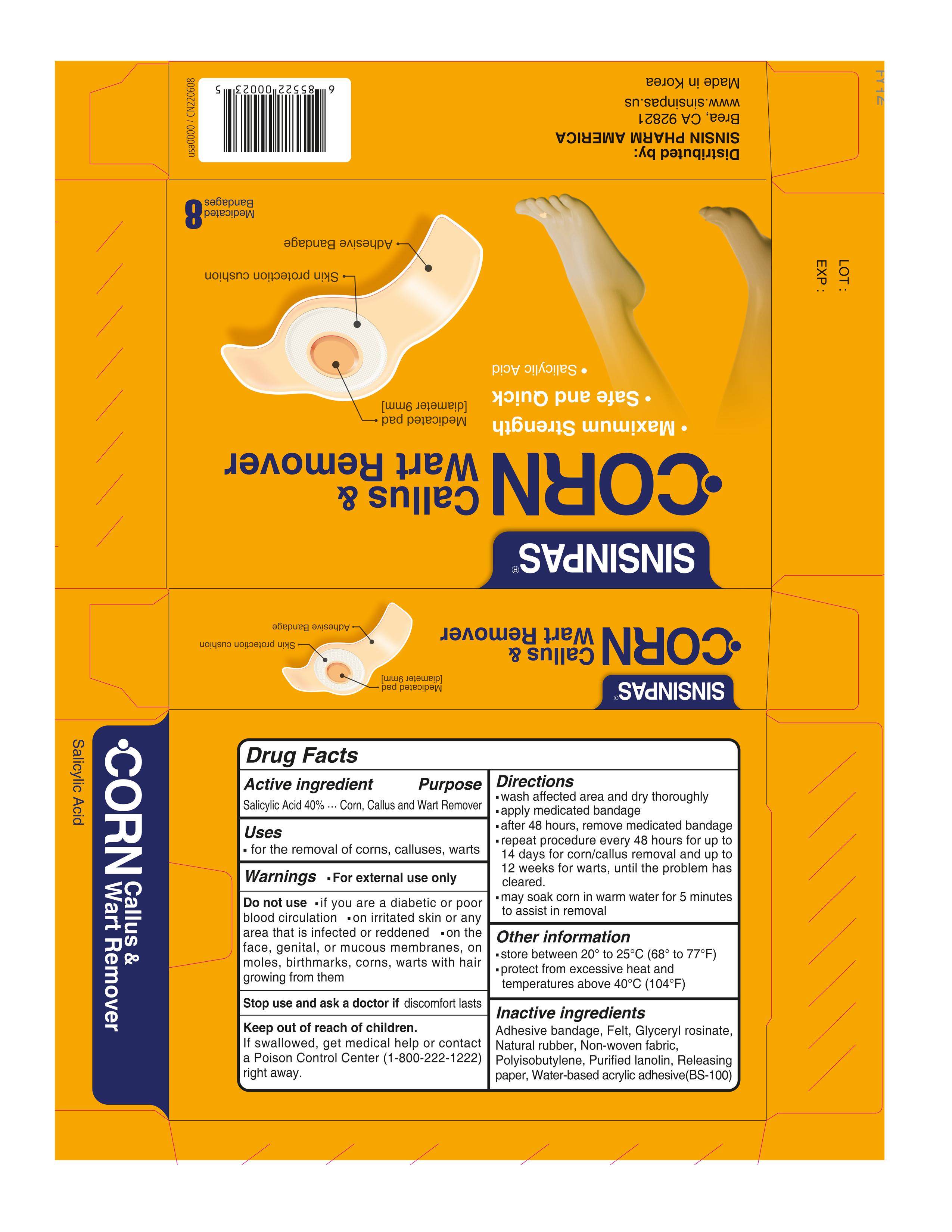 DRUG LABEL: SINSINPAS CORN REMOVER
NDC: 55264-115 | Form: PATCH
Manufacturer: Sinsin Pharmaceutical Co., Ltd.
Category: otc | Type: HUMAN OTC DRUG LABEL
Date: 20251007

ACTIVE INGREDIENTS: SALICYLIC ACID 25.6 mg/100 1
INACTIVE INGREDIENTS: GLYCERYL ROSINATE; NATURAL LATEX RUBBER; LANOLIN; POLYISOBUTYLENE (1000 MW)

SINSINPAS CORN REMOVER PATCH

Active ingredients

Salicylic Acid 40% ------------------------------ Corn, Callus and Wart Remover

Purpose

Corn, Callus and Wart Remover

Uses

- for the removal of corns, calluses, warts

Warnings

- For external use only

Do not use

- if you are a diabetic or poor blood circulation

- on irritated skin or any area that is infected or reddened

- on the face, genital, or mucous membranes, on moles, birthmarks, corns, warts with hair growing from them

Stop use and ask a doctor ifdiscomfort persists

Keep out of reach of children

If swallowed, get medical help or contact a Poison Control Center (1-800-222-1222) right away.

Directions

- wash affected area and dry thoroughly

- apply medicated bandage

- after 48 hours, remove medicated bandage

- repeat procedure every 48 hours for up to 14 days for corn/callus removal and up to 12 weeks for warts, until the problem has cleared.

- may soak corn in warm water for 5 minutes to assist in removal

Other information

- store between 20℃ to 25℃ (68℉ to 77℉)

- protect from excessive heat and temperatures above 40℃ (104℉)

Inactive ingredients

Adhesive bandage, Felt, Glyceryl rosinate, Natural rubber, Non-woven fabric, Polyisobutylene, Purified lanolin, Releasing paper, Water-based acrylic adhesive(BS-100)